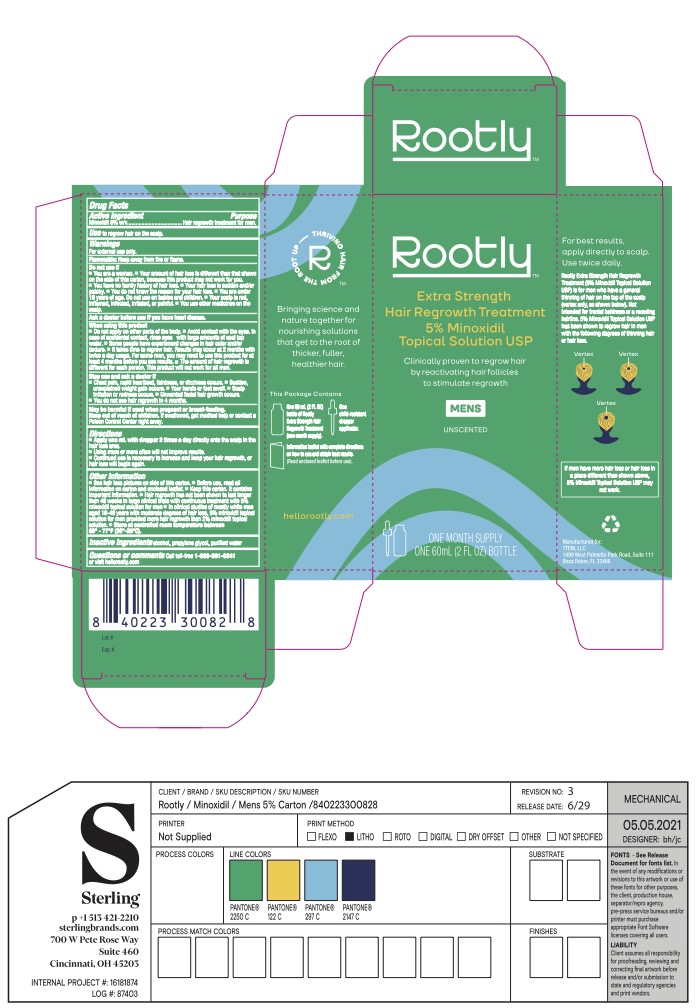 DRUG LABEL: Rootly Extra Strength Hair Regrowth Treatment for Men
NDC: 70150-005 | Form: SOLUTION
Manufacturer: TTEM, LLC
Category: otc | Type: HUMAN OTC DRUG LABEL
Date: 20230118

ACTIVE INGREDIENTS: MINOXIDIL 5 g/100 mL
INACTIVE INGREDIENTS: PROPYLENE GLYCOL; WATER; ISOPROPYL ALCOHOL

Rootly Extra Strength Hair Regrowth Treatment for Men

ACTIVE INGREDIENT

Minoxidil 5% w/v

PURPOSE

Hair regrowth treatment for men

USE

to regrow hair on the top of the scalp

WARNINGS

For external use only.

Flammable: Keep away from fire or flame.

Do not use if

- You are a woman
- Your degree of hair loss is different than that shown on this carton, because this product may not work for you
- You have no family history of hair loss
- Your hair loss is sudden and/or patchy
- Your hair loss is associated with childbirth
- You do not know the reason for your hair loss
- You are under 18 years of age. Do not use on babies or children.
- Your scalp is red, inflammed, infected, irritated, or painful
- You use other medicines on your scalp

Ask a doctor before use if you have heart disease

When using this product

- Do not apply on other parts of the body
- Avoid contact with eyes. In case of accidental contact, rinse eyes with large amounts of cool tap water.
- Some people have experienced change in hair color and/or texture. It takes time to regrow hair. For some men, you may need to use this product 2 times a day for at least 4 months before you see results.
- The amount of hair regrowth is different for each person. This product will not work for all men.

Stop use and ask doctor if

- chest pain, rapid heartbeat, faintness, or dizziness occurs
- sudden, unexplained weight gain occurs
- your hands or feet swell
- scalp irritation or redness occurs
- unwanted facial hair growth occurs
- you do not see hair regrowth in 4 months

PREGNANCY OR BREAST FEEDING

May be harmful if used when pregnant or breast-feeding.

KEEP OUT OF REACH OF CHILDREN

If swallowed, get medical help or contact a Poison Control Center right away.

DIRECTIONS

• apply one mL with dropper 2 times a day directly onto the scalp in the hair loss area

• using more or more often will not improve results

• continued use is necessary to increase and keep your hair regrowth, or hair loss will begin again

OTHER INFORMATION

• see hair loss pictures on side of this carton

• before use, read all information on carton and enclosed leaflet

• keep the carton. It contains important information.

• hair regrowth has not been shown to last longer than 48 weeks in large clinical trials with continuous treatment with 5% minoxidil topical solution for men

• in clinical studies of mostly white men aged 18-49 years with moderate degrees of hair loss, 5% minoxidil topical solution for men provided more hair regrowth than 2% minoxidil topical solution

• store at controlled room temperature 68º to 77ºF (20º to 25ºC).

INACTIVE INGREDIENT

lcohol, Propylene Glycol, Purified Water

Questions or comments

Call toll-free 1-800-681-0241 or visit hellorootly.com